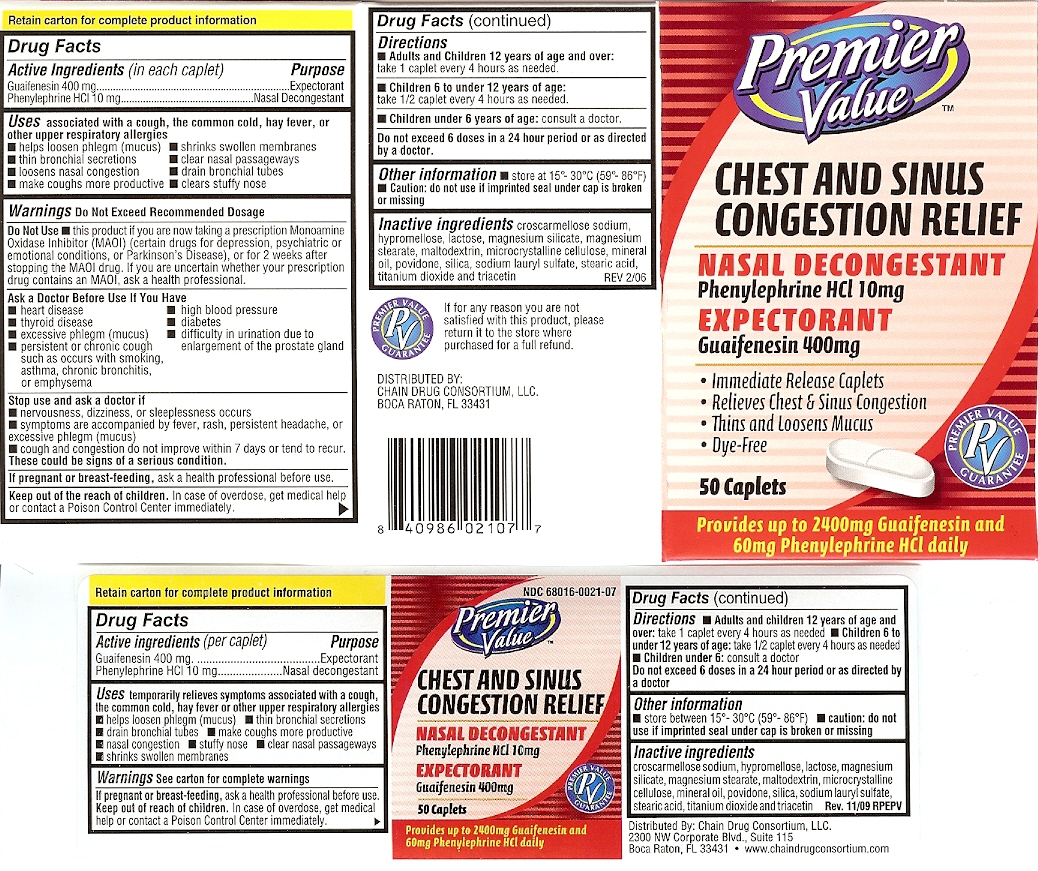 DRUG LABEL: Premier Value Chest and Sinus Congestion relief
NDC: 68016-021 | Form: TABLET
Manufacturer: Chain Drug Consortium, LLC
Category: otc | Type: HUMAN OTC DRUG LABEL
Date: 20151009

ACTIVE INGREDIENTS: Guaifenesin 400 mg/1 1; PHENYLEPHRINE HYDROCHLORIDE 10 mg/1 1
INACTIVE INGREDIENTS: CROSCARMELLOSE SODIUM; LACTOSE; MAGNESIUM STEARATE; MALTODEXTRIN; CELLULOSE, MICROCRYSTALLINE; POVIDONE; MAGNESIUM SILICATE

DRUG FACTS

ACTIVE INGREDIENT

Guaifenesin 400 mg
Phenylephrine HCl 10 mg

PURPOSE

Guaifenesin Expectorant
Phenylephrine HCl Nasal decongestant

INDICATIONS AND USAGE

temporarily relieves symptoms associated with a cough ,the common cold,hay fever or other upper respiratory allergies.
helps loosen phlegm;mucus
clear nasal passageways
loosens nasal congestion
drain bronchial tubes
shrinks swollen membranes
clears stuffy nose
makes coughs more productive

WARNINGS

do not exceed recommended dosage

Do not use this product if you are now taking a prescription Monoamine Oxidase inhibitor ; MAIO,
certain drugs for depression,psychiatric or emotional conditions, or Parkinsons Disease or for 2 weeks
after stopping the MAIO drug,if you are uncertain whether your prescription contains an MAIO ,
ask a health professional.

ask a doctor before use if you have
heart disease
high blood pressure
thyroid disease
diabetes
excessive phlegm;mucus
difficulty in urination due to an enlarged prostate gland
persistent or chronic cough such as occurs with smoking,asthma,chronic bronchitis or emphysema

stop use and ask a doctor if
nervousness,dizziness or sleeplessness occurs
symptoms are accompanied by fever,rash,persistent headache or excessive phlegm;mucus.
cough and congestion do not approve within 7 days or tend to recur
these could be signs of a serious condition

PREGNANCY OR BREAST FEEDING

ask a health professional before use.

KEEP OUT OF REACH OF CHILDREN

in case of overdose,get medical help or contact a Poison Control Center immediately.

directions
Adults and Children 12 years of age and over take 1 caplet every 4 hours as needed
children 6 to under 12 years of age consult a doctor
do not exceed 6 doses in a 24 hour period or as directed by a doctor.

INACTIVE INGREDIENT

croscarmellose sodium,hypromellose,lactose,magnesium silicate,
magnesium stearate,maltodextrin,mycocrystalline cellulose,mineral oil,povidone,
silica,sodium lauryl sulfate,stearic acid,titanium oxide and triacetin.